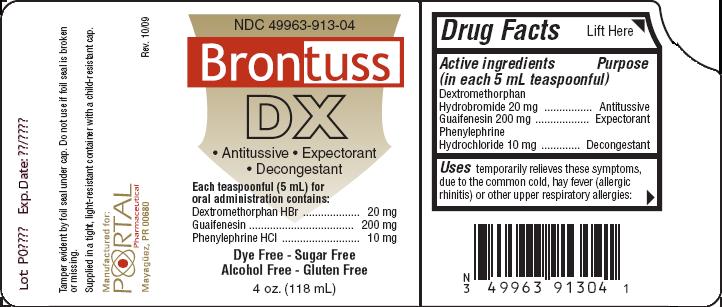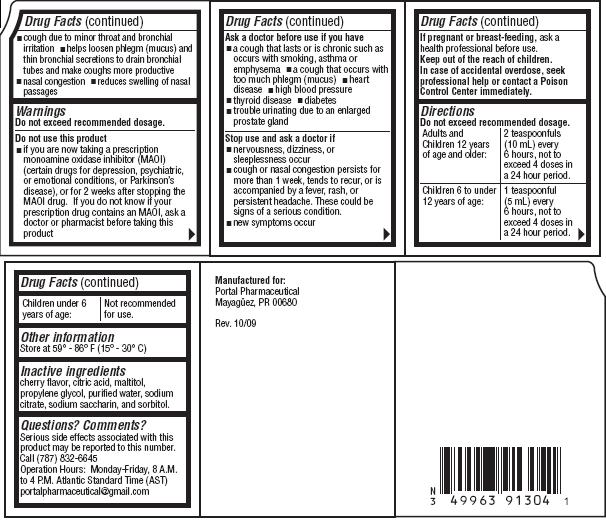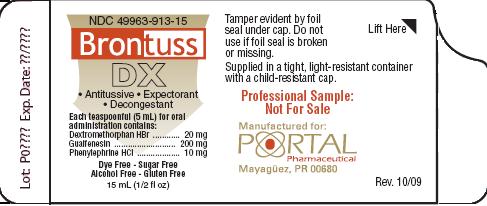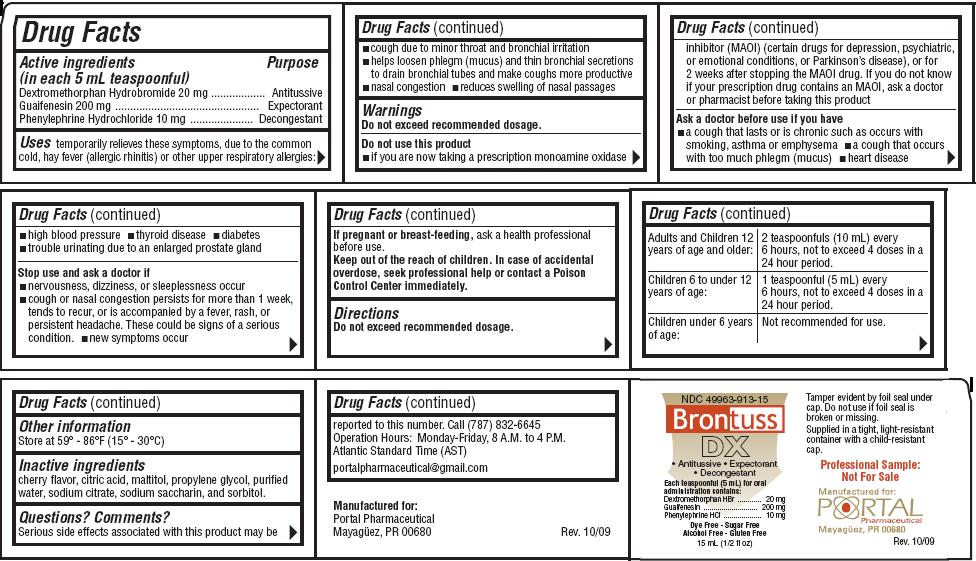 DRUG LABEL: Brontuss
NDC: 49963-913 | Form: LIQUID
Manufacturer: Portal Inc.
Category: otc | Type: HUMAN OTC DRUG LABEL
Date: 20091217

ACTIVE INGREDIENTS: Dextromethorphan Hydrobromide 20 mg/5 mL; Guaifenesin 200 mg/5 mL; Phenylephrine Hydrochloride 10 mg/5 mL

Brontuss DX

Drug Facts

Active ingredients Purpose
(in each 5 mL teaspoonful)
Dextromethorphan Hydrobromide 20 mg...... Antitussive
Guaifenesin 200 mg................................ Expectorant
Phenylephrine Hydrochloride 10 mg..........Decongestant

Uses

temporarily relieves these symptoms, due to the common cold, hay fever (allergic rhinitis) or other upper respiratory allergies:

- cough due to minor throat and bronchial irritation
- helps loosen phlegm (mucus) and thin bronchial secretions to drain bronchial tubes and make coughs more productive
- nasal congestion
- reduces swelling of nasal passages

Warnings

Do not exceed recommended dosage.

Do not use this product

- if you are now taking a prescription monoamine oxidase inhibitor (MAOI) (certain drugs for depression, psychiatric, or emotional conditions, or Parkinson's disease), or for 2 weeks after stopping the MAOI drug. If you do not know if your prescription drug contains an MAOI, ask a doctor or pharmacist before taking this product

Ask a doctor before use if you have

- a cough that lasts or is chronic such as occurs with smoking, asthma or emphysema
- a cough that occurs with too much phlegm (mucus)
- heart disease
- high blood pressure
- thyroid disease
- diabetes
- trouble urinating due to an enlarged prostate gland

Stop use and ask a doctor if

- nervousness, dizziness, or sleeplessness occur
- cough or nasal congestion persists for more than 1 week, tends to recur, or is accompanied by a fever, rash, or persistent headache. These could be signs of a serious condition.
- new symptoms occur

If pregnant or breast-feeding,

ask a health professional before use.

Keep out of reach of children.

In case of accidental overdose, seek professional help or contact a Poison Control Center immediately.

Directions

Do not exceed recommended dosage.

Adults and Children 12 years of age and older: | 2 teaspoonfuls (10mL) every 6 hours, not to exceed 4 doses in a 24 hour period.
Children 6 to under 12 years of age: | 1 teaspoonful (5 mL) every 6 hours, not to exceed 4 doses in a 24 hour period.
Children under 6 years of age: | Not recommended for use.

Other information

Store at 59o-86oF (15o-30oC)

Inactive ingredients

cherry flavor, citric acid, maltitol, propylene glycol, purified water, sodium citrate, sodium saccharin, and sorbitol.

Questions? Comments?

Serious side effects associated with this product may be reported to this number.
Call (787)832-6645
Operation Hours: Monday - Friday, 8 A.M. to 4 P.M. Atlantic Standard Time (AST)
portalpharmaceutical@gmail.com
Manufactured for:
Portal Pharmaceutical
Mayaguez, PR 00680
Rev. 10/09

PRODUCT PACKAGING:

The packaging below represents the labeling currently used:
Principal Display Panel and Side Panel for 118mL Label:
NDC 49963-913-04
Brontuss
DX
Antitussive / Expectorant
Decongestant
Each teaspoonful (5 mL) for oral administration contains:
Dextromethorphan HBr.............. 20 mg
Guaifenesin.............................200 mg
Phenylephrine HCl.................... 10 mg
Dye Free - Sugar Free
Alcohol Free - Gluten Free
4 oz. (118 mL)
Tamper evident by foil seal under cap. Do not use if foil seal is broken or missing.
Supplied in a tight, light-resistant container with a child-resistant cap.
Manufactured for:
Portal Pharmaceutical
Mayaguez, PR 00680
Rev. 10/09
Principal Display Panel and Side Panel for 15 mL Label:
NDC 49963-913-15
Brontuss
DX
Antitussive / Expectorant
Decongestant
Each teaspoonful (5 mL) for oral administration contains:
Dextromethorphan HBr.......... 20 mg
Guaifenesin........................ 200 mg
Phenylephrine HCl................ 10 mg
Dye Free / Sugar Free
Alcohol Free / Gluten Free
15 mL (1/2 fl oz)
Tamper evident by foil seal under cap. Do not use if foil seal is broken or missing.
Supplied in a tight, light-resistant container with a child-resistant cap.
Professional Sample:
Not For Sale
Manufactured for:
Portal Pharmaceutical
Mayaguez, PR 00680
Rev. 10/09